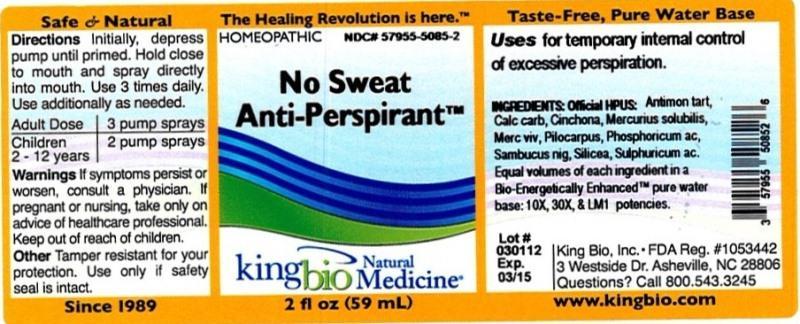 DRUG LABEL: No Sweat Anti Perspirant
NDC: 57955-5085 | Form: LIQUID
Manufacturer: King Bio Inc.
Category: homeopathic | Type: HUMAN OTC DRUG LABEL
Date: 20120917

ACTIVE INGREDIENTS: ANTIMONY POTASSIUM TARTRATE 10 [hp_X]/59 mL; OYSTER SHELL CALCIUM CARBONATE, CRUDE 10 [hp_X]/59 mL; CINCHONA OFFICINALIS BARK 10 [hp_X]/59 mL; MERCURIUS SOLUBILIS 10 [hp_X]/59 mL; PILOCARPUS JABORANDI LEAF 10 [hp_X]/59 mL; PHOSPHORIC ACID 10 [hp_X]/59 mL; SAMBUCUS NIGRA FLOWERING TOP 10 [hp_X]/59 mL; SILICON DIOXIDE 10 [hp_X]/59 mL; SULFURIC ACID 10 [hp_X]/59 mL
INACTIVE INGREDIENTS: WATER

No Sweat Anti-Perspirant

Active Ingredients

Official HPUS: Antimonium tartaricum, Calcarea carbonica, Cinchona officinalis, Mercurius solubilis, Mercurius vivus, Pilocarpus, Phosphoricum acidum, Sambucus nigra, Silicea and Sulphuricum acidum.

Inactive Ingredient

Equal volumes of each ingredient in a Bio-Energetically Enhanced pure water base: 10X, 30X, and LM1 potencies.

Purpose

Uses for temporary internal control of excessive perspiration.

Dosage and Administration

Directions Initially, depress pump until primed. Hold close to mouth and spray directly into mouth. Use 3 times daily. Use additionally as needed.

Adult Dose 3 pump sprays

Children 2 - 12 years 2 pump sprays

Warnings

If symptoms persist or worsen, consult a physician. If pregnant or nursing, take only on advice of healthcare professional. Keep out of reach of children.

Other: Tamper resistant for your protection. Use only if safety seal is intact.

Keep out of reach of children.

Indications and Usage

Uses for temporary internal control of excessive perspiration.

PACKAGE LABEL

King Bio Inc.

3 Westside Drive

Asheville, NC 28806

Questions? Call 800.543.3245

www.kingbio.com